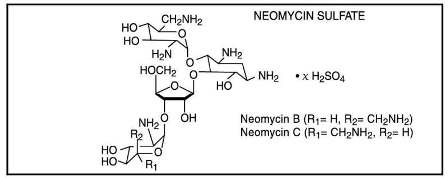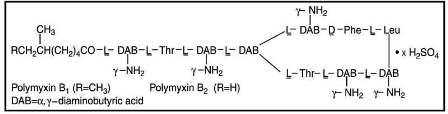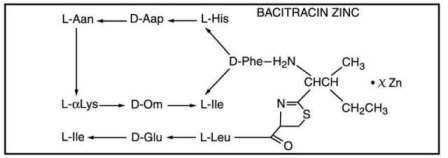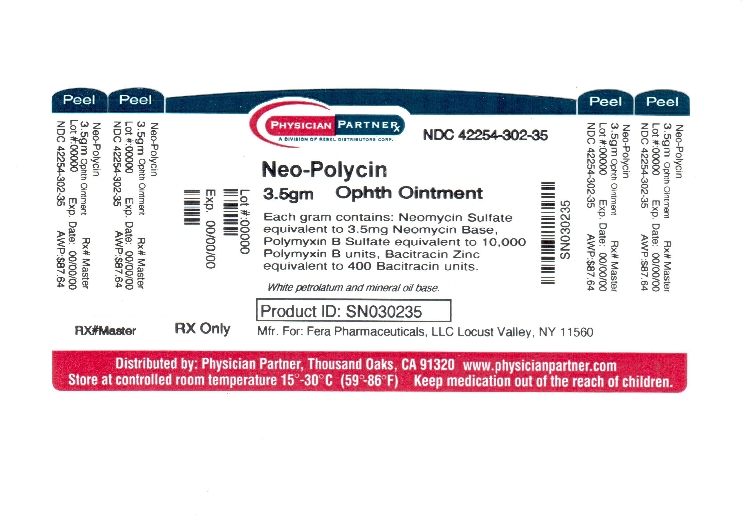 DRUG LABEL: NEO-POLYCIN
NDC: 42254-302 | Form: OINTMENT
Manufacturer: Rebel Distributors Corp
Category: prescription | Type: HUMAN PRESCRIPTION DRUG LABEL
Date: 20120926

ACTIVE INGREDIENTS: NEOMYCIN SULFATE 3.5 mg/1 g; POLYMYXIN B SULFATE 10000 U/1 g; BACITRACIN ZINC 400 U/1 g
INACTIVE INGREDIENTS: MINERAL OIL; PETROLATUM

NEO-POLYCIN

DESCRIPTION:

Neomycin and polymyxin B sulfates and bacitracin zinc ophthalmic ointment is a sterile antimicrobial ointment for ophthalmic use. Each gram contains: neomycin sulfate equivalent to 3.5 mg neomycin base, polymyxin B sulfate equivalent to 10,000 polymyxin B units, bacitracin zinc equivalent to 400 bacitracin units in a white petrolatum and mineral oil base.

Neomycin sulfate is the sulfate salt of neomycin B and C, which are produced by the growth of Streptomyces fradiae Waksman (Fam. Streptomycetaceae). It has a potency equivalent of not less than 600 µg of neomycin standard per mg, calculated on an anhydrous basis. The structural formulae are:

Polymyxin B sulfate is the sulfate salt of polymyxin B1 and B2, which are produced by the growth of Bacillus polymyxa (Prazmowski) Migula (Fam. Bacillaceae). It has a potency of not less than 6,000 polymyxin B units per mg, calculated on an anhydrous basis. The structural formulae are:

Bacitracin zinc is the zinc salt of bacitracin, a mixture of related cyclic polypeptides (mainly bacitracin A) produced by the growth of an organism of the

licheniformis

group of

Bacillus subtilis

var Tracy. It has a potency of not less than 40 bacitracin units per mg. The structural formula is:

CLINICAL PHARMACOLOGY:

A wide range of antibacterial action is provided by the overlapping spectra of neomycin, polymyxin B sulfate, and bacitracin.

Neomycin is bactericidal for many gram-positive and gram-negative organisms. It is an aminoglycoside antibiotic which inhibits protein synthesis by binding with ribosomal RNA and causing misreading of the bacterial genetic code.

Polymyxin B is bactericidal for a variety of gram-negative organisms. It increases the permeability of the bacterial cell membrane by interacting with the phospholipid components of the membrane.

Bacitracin is bactericidal for a variety of gram-positive and gram-negative organisms. It interferes with bacterial cell wall synthesis by inhibition of the regeneration of phospholipid receptors involved in peptidoglycan synthesis.

Microbiology:

Neomycin sulfate, polymyxin B sulfate, and bacitracin zinc together are considered active against the following microorganisms: Staphylococcus aureus, streptococci including Streptococcus pneumoniae, Escherichia coli, Haemophilus influenzae, Klebsiella/Enterobacter species, Neisseria species, and Pseudomonas aeruginosa. The product does not provide adequate coverage against Serratia marcescens .

INDICATIONS AND USAGE:

Neo-PolycinTM Ophthalmic Ointment is indicated for the topical treatment of superficial infections of the external eye and its adnexa caused by susceptible bacteria. Such infections encompass conjunctivitis, keratitis, and keratoconjunctivitis, blepharitis and blepharoconjunctivitis.

CONTRAINDICATIONS:

Neo-PolycinTM Ophthalmic Ointment is contraindicated in individuals who have shown hypersensitivity to any of its components.

WARNINGS:

NOT FOR INJECTION INTO THE EYE. Neomycin and polymyxin B sulfates and bacitracin zinc ophthalmic ointment should never be directly introduced into the anterior chamber of the eye. Ophthalmic ointments may retard corneal wound healing. Topical antibiotics, particularly neomycin sulfate, may cause cutaneous sensitization. A precise incidence of hypersensitivity reactions (primarily skin rash) due to topical antibiotics is not known. The manifestations of sensitization to topical antibiotics are usually itching, reddening, and edema of the conjunctiva and eyelid. A sensitization reaction may manifest simply as a failure to heal. During long-term use of topical antibiotic products, periodic examination for such signs is advisable, and the patient should be told to discontinue the product if they are observed. Symptoms usually subside quickly on withdrawing the medication. Applications of products containing these ingredients should be avoided for the patient thereafter (see PRECAUTIONS: General).

PRECAUTIONS:

General:

As with other antibiotic preparations, prolonged use of neomycin and polymyxin B sulfates and bacitracin zinc ophthalmic ointment may result in overgrowth of nonsusceptible organisms including fungi. If superinfection occurs, appropriate measures should be initiated. Bacterial resistance to neomycin and polymyxin B sulfates and bacitracin zinc ophthalmic ointment may also develop. If purulent discharge, inflammation, or pain becomes aggravated, the patient should discontinue use of the medication and consult a physician. There have been reports of bacterial keratitis associated with the use of topical ophthalmic products in multiple-dose containers which have been inadvertently contaminated by patients, most of whom had a concurrent corneal disease or a disruption of the ocular epithelial surface (see PRECAUTIONS: Information for Patients). Allergic cross-reactions may occur which could prevent the use of any or all of the following antibiotics for the treatment of future infections: Kanamycin, paromomycin, streptomycin, and possibly gentamicin.

Information for Patients:

Patients should be instructed to avoid allowing the tip of the dispensing container to contact the eye, eyelid, fingers, or any other surface. The use of this product by more than one person may spread infection. Patients should also be instructed that ocular products, if handled improperly, can become contaminated by common bacteria known to cause ocular infections. Serious damage to the eye and subsequent loss of vision may result from using contaminated products (see PRECAUTIONS: General). If the condition persists or gets worse, or if a rash or allergic reaction develops, the patient should be advised to stop use and consult a physician. Do not use this product if you are allergic to any of the listed ingredients. Keep tightly closed when not in use. Keep out of reach of children.

Carcinogenesis, Mutagenesis, Impairment of Fertility:

Long-term studies in animals to evaluate carcinogenic or mutagenic potential have not been conducted with polymyxin B sulfate or bacitracin. Treatment of cultured human lymphocytes in vitro with neomycin increased the frequency of chromosome aberrations at the highest concentration (80 µg/mL) tested; however, the effects of neomycin on carcinogenesis and mutagenesis in humans are unknown. Polymyxin B has been reported to impair the motility of equine sperm, but its effects on male or female fertility are unknown. No adverse effects on male or female fertility, litter size, or survival were observed in rabbits given bacitracin zinc 100 gm/ton of diet.

Teratogenic Effects: Pregnancy Category C.

Animal reproduction studies have not been conducted with neomycin sulfate, polymyxin B sulfate or bacitracin. It is also not known whether neomycin and polymyxin B sulfates and bacitracin zinc ophthalmic ointment can cause fetal harm when administered to a pregnant woman or can affect reproduction capacity. Neoymcin and polymyxin B sulfates and bacitracin zinc ophthalmic ointment should be given to a pregnant woman only if clearly needed.

Nursing Mothers:

It is not known whether this drug is excreted in human milk. Because many drugs are excreted in human milk, caution should be exercised when neomycin and polymyxin B sulfates and bacitracin zinc ophthalmic ointment is administered to a nursing woman.

Pediatric Use:

Safety and effectiveness in pediatric patients have not been established.

Geriatric Use:

No overall differences in safety or effectiveness have been observed between elderly and younger patients.

ADVERSE REACTIONS:

Adverse reactions have occurred with the anti-infective components of neomycin and polymyxin B sulfates and bacitracin zinc ophthalmic ointment. The exact incidence is not known. Reactions occurring most often are allergic sensitization reactions including itching, swelling, and conjunctival erythema (see WARNINGS). More serious hypersensitivity reactions, including anaphylaxis, have been reported rarely. Local irritation on instillation has also been reported.

To report SUSPECTED ADVERSE REACTIONS, contact Fera Pharmaceuticals, LLC at (414) 434-6604, Monday-Friday 9am-5pm EST or FDA at 1-800-FDA-1088 or www.fda.gov/medwatch.

DOSAGE AND ADMINISTRATION:

May be applied every 3 or 4 hours for 7 to 10 days, depending on the severity of the infection.

HOW SUPPLIED:

Neo-PolycinTM Ophthalmic Ointment is supplied in 3.5 g (1/8 oz) sterile tamper evident tubes with ophthalmic tip.

NDC 42254-302-35

Store at 20o-25oC (68o-77oF) [See USP Controlled room temperature].

Neo-Polycin is a Trademark of Fera Pharmaceuticals, LLC.

FERA

Mfd. for:

Fera Pharmaceuticals, LLC

Locust Valley, NY 11560

Repackaged by:

Rebel Distributors Corp.

Thousand Oaks, CA 91320